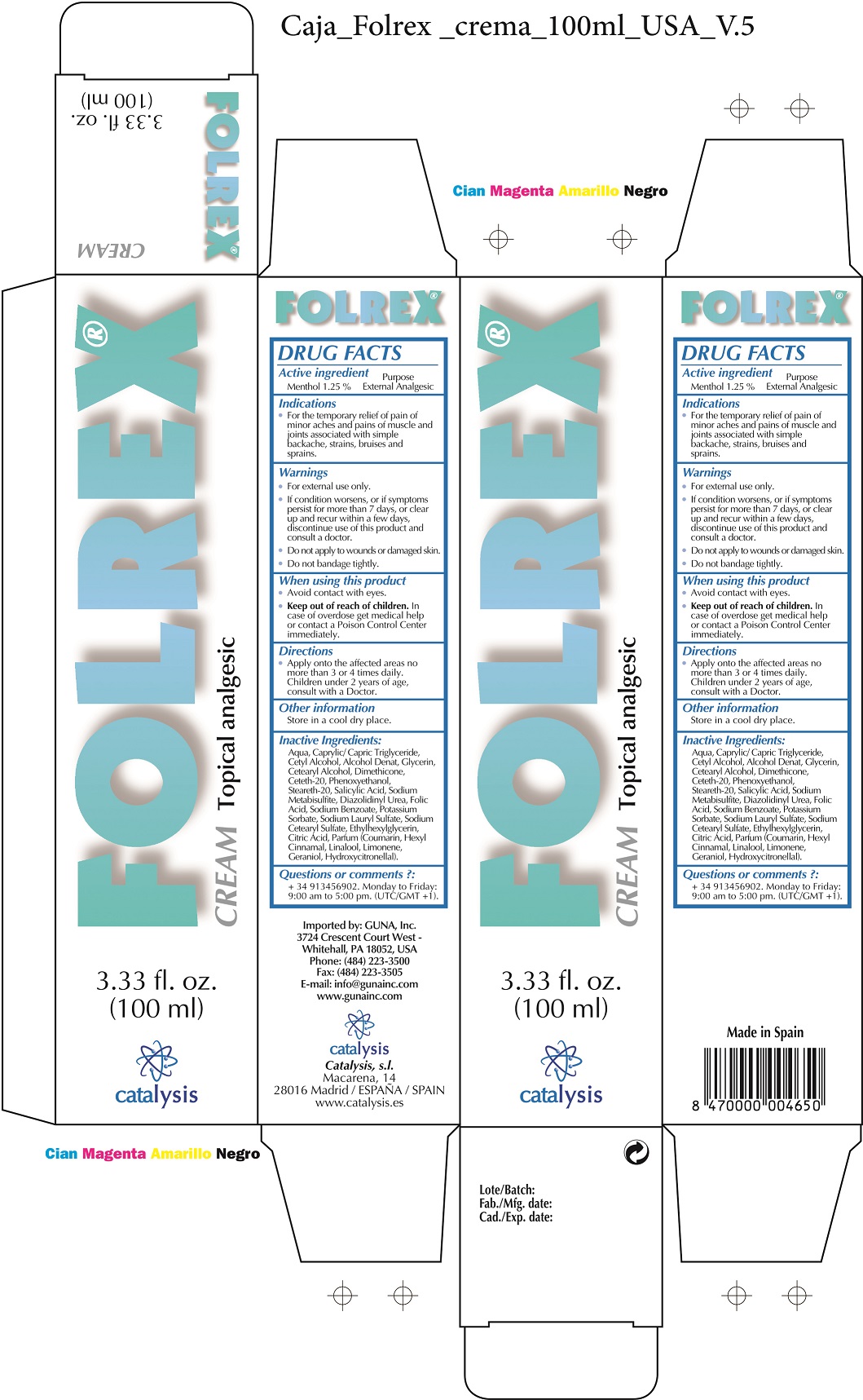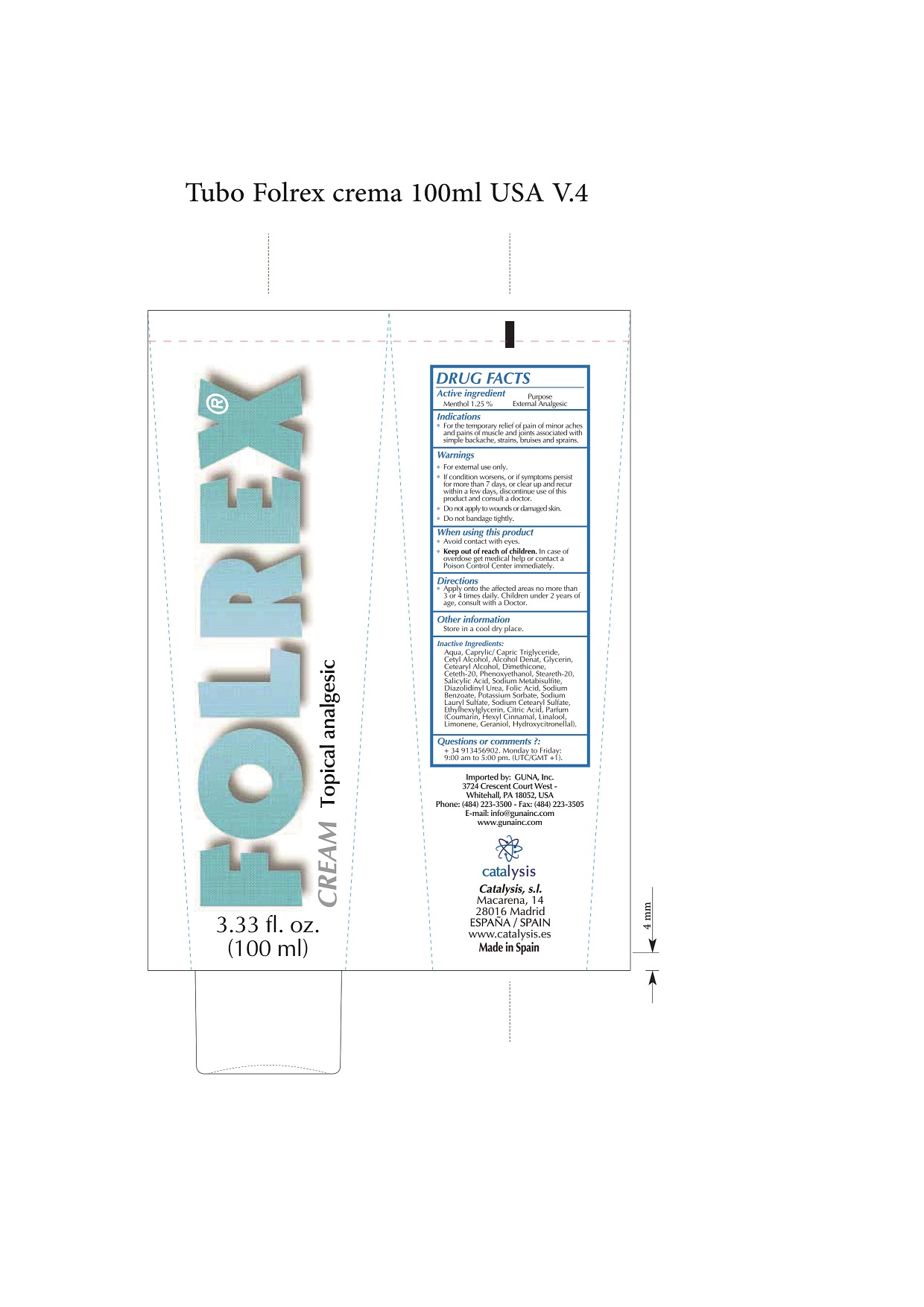 DRUG LABEL: Folrex Cream
NDC: 64539-014 | Form: CREAM
Manufacturer: Catalysis, SL
Category: otc | Type: HUMAN OTC DRUG LABEL
Date: 20180309

ACTIVE INGREDIENTS: MENTHOL 1.25 mg/1 mL
INACTIVE INGREDIENTS: DIAZOLIDINYL UREA 0.3 mg/1 mL; POTASSIUM SORBATE 0.1 mg/1 mL; CAPRYLIC/CAPRIC/LAURIC TRIGLYCERIDE 10 mg/1 mL; CETETH-20 1.221 mg/1 mL; STEARETH-20 0.521 mg/1 mL; SODIUM LAURYL SULFATE 0.09 mg/1 mL; GLYCERIN 3 mg/1 mL; DIMETHICONE 1.5 mg/1 mL; SALICYLIC ACID 0.5 mg/1 mL; SODIUM METABISULFITE 0.3 mg/1 mL; FOLIC ACID 0.114 mg/1 mL; COUMARIN 0.1 mg/1 mL; .ALPHA.-HEXYLCINNAMALDEHYDE 0.1 mg/1 mL; CETYL ALCOHOL 5.257 mg/1 mL; LINALOOL, (-)- 0.1 mg/1 mL; LIMONENE, (+)- 0.1 mg/1 mL; PHENOXYETHANOL 0.72 mg/1 mL; ETHYLHEXYLGLYCERIN 0.08 mg/1 mL; GERANIOL 0.1 mg/1 mL; HYDROXYCITRONELLAL 0.1 mg/1 mL; SODIUM BENZOATE 0.1 mg/1 mL; CITRIC ACID MONOHYDRATE 0.08 mg/1 mL; WATER 100 mg/1 mL; ALCOHOL 5 mg/1 mL

Folrex Cream

ACTIVE INGREDIENTS PURPOSE

Menthol 1.25%.................. External Analgesic

Warnings

- For external use only.
- If conditions worsens, or if symptons persists for more than 7 days or clear up and recur within a few days, discontinue use of this product and consult a doctor.
- Do not apply to wounds or damaged skins.
- Do not bandaged tightly

WARNINGS

- Avoid contact with eyes
- Keep out of the reach of children. In case of overdose,get medical help or contact a Poison Control Medical Center inmediately

Warnings

Keep out of reach of children

Questions or comments?

+ 34 91 345 6902 M-F 9:00 am to 5:00 pm

Other Information

. keep the product in a cool and dry place

Directions

- apply onto the affected area not more than 3 or 4 times daily
- Children under 4 years old, consult with a Doctor.

DOSAGE AND ADMINISTRATION

- apply onto the affected area not more than 3 or 4 times daily
- Children under 4 years old, consult with a Doctor.

Uses

- For the temporary relief of pains of minor aches and pain of muscles and joints associated with:
- Simple backage, strains, bruises and sprains

Inactive Ingredients

Aqua, Caprylic/Capric Triglyceride, Cetyl Alcohol, Alcohol Denat, Glycerin, Cetearyl Alcohol, Dimethicone, Menthol, Ceteth-20, Phenoxyethanol., Steareth-20, Salicylic Acid , Sodium Metabisulfite, Diazolidinyl Urea, Folic Acid, Sodium Benzoate, Potassium Sorbate, Sodium Lauryl Sulfate, Sodium Cetearyl Sulfate, Ethylhexylglycerin., Citric Acid., Parfum. Coumarin, Hexyl Cinnamal, Linalool, Limonene, Geraniol, Hydroxycitronellal

Uses

For the temporary relief of pains of minor aches and pain of muscles and joints associated with:
Simple backage, strains, bruises and sprains